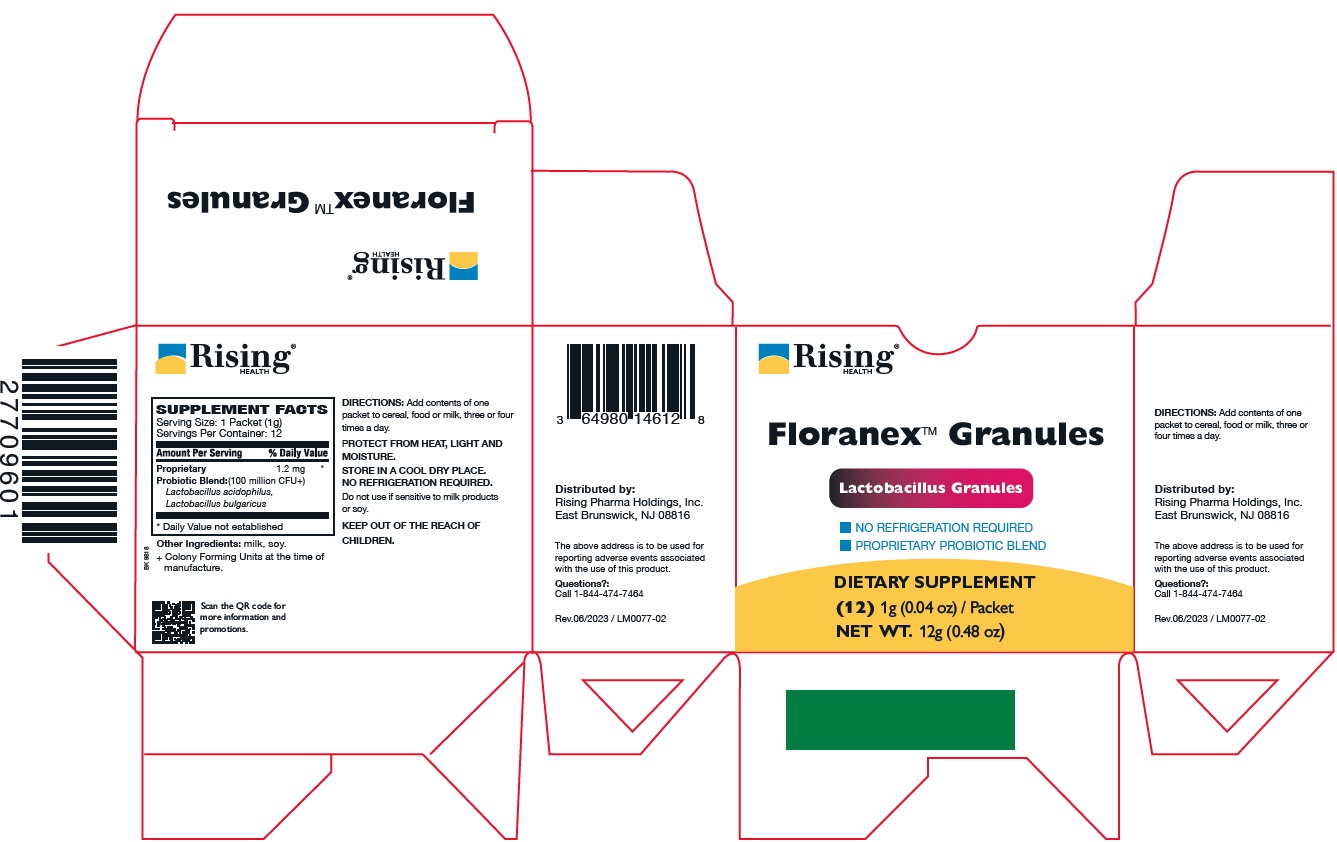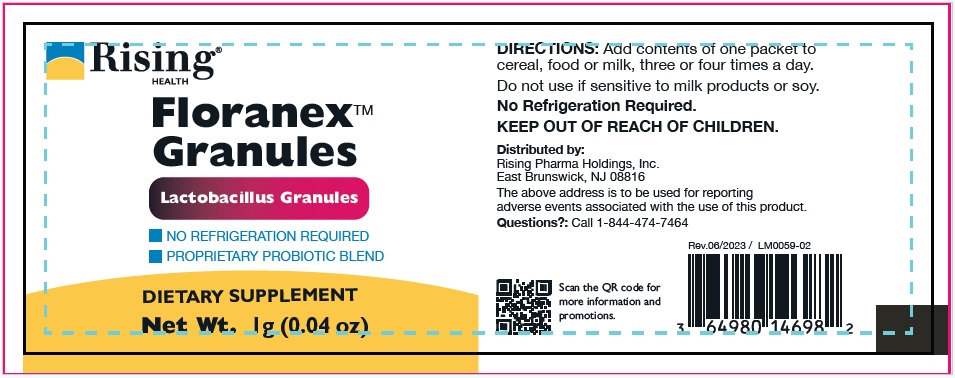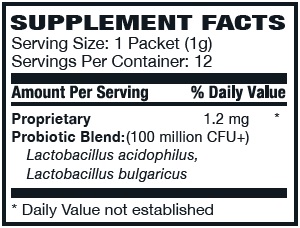 DRUG LABEL: Floranex Granules
NDC: 64980-146 | Form: GRANULE
Manufacturer: Rising Pharma Holdings, Inc.
Category: other | Type: DIETARY SUPPLEMENT
Date: 20250619

ACTIVE INGREDIENTS: LACTOBACILLUS ACIDOPHILUS 100000000 [CFU]/1 g; LACTOBACILLUS DELBRUECKII BULGARICUS 100000000 [CFU]/1 g

FloranexTM Granules, DIETARY SUPPLEMENT, (12) 1g (0.04 oz) / Packet, NET WT. 12g (0.48 oz)

STATEMENT OF IDENTITY

Other Ingredients: milk, soy.
+ Colony Forming Units at the time of manufacture.

DOSAGE AND ADMINISTRATION

DIRECTIONS: Add contents of one packet to cereal, food or milk, three or four times a day.

SAFE HANDLING WARNING

PROTECT FROM HEAT, LIGHT AND MOISTURE.
STORE IN A COOL DRY PLACE.
NO REFRIGERATION REQUIRED.
Do not use if sensitive to milk products or soy.
KEEP OUT OF THE REACH OF CHILDREN.

Distributed by:
Rising Pharma Holdings, Inc.
East Brunswick, NJ 08816

The above address is to be used for reporting adverse events associated with the use of this product.

Questions?:
Call 1-844-474-7464
Rev.06/2023 / LM0077-02

PACKAGE LABEL

Floranex™ Granules

DIETARY SUPPLEMENT

(12) 1g (0.04 oz) / Packet
NET WT. 12g (0.48 oz)

Packet label (64980-146-98)

Carton Label (64980-146-12)